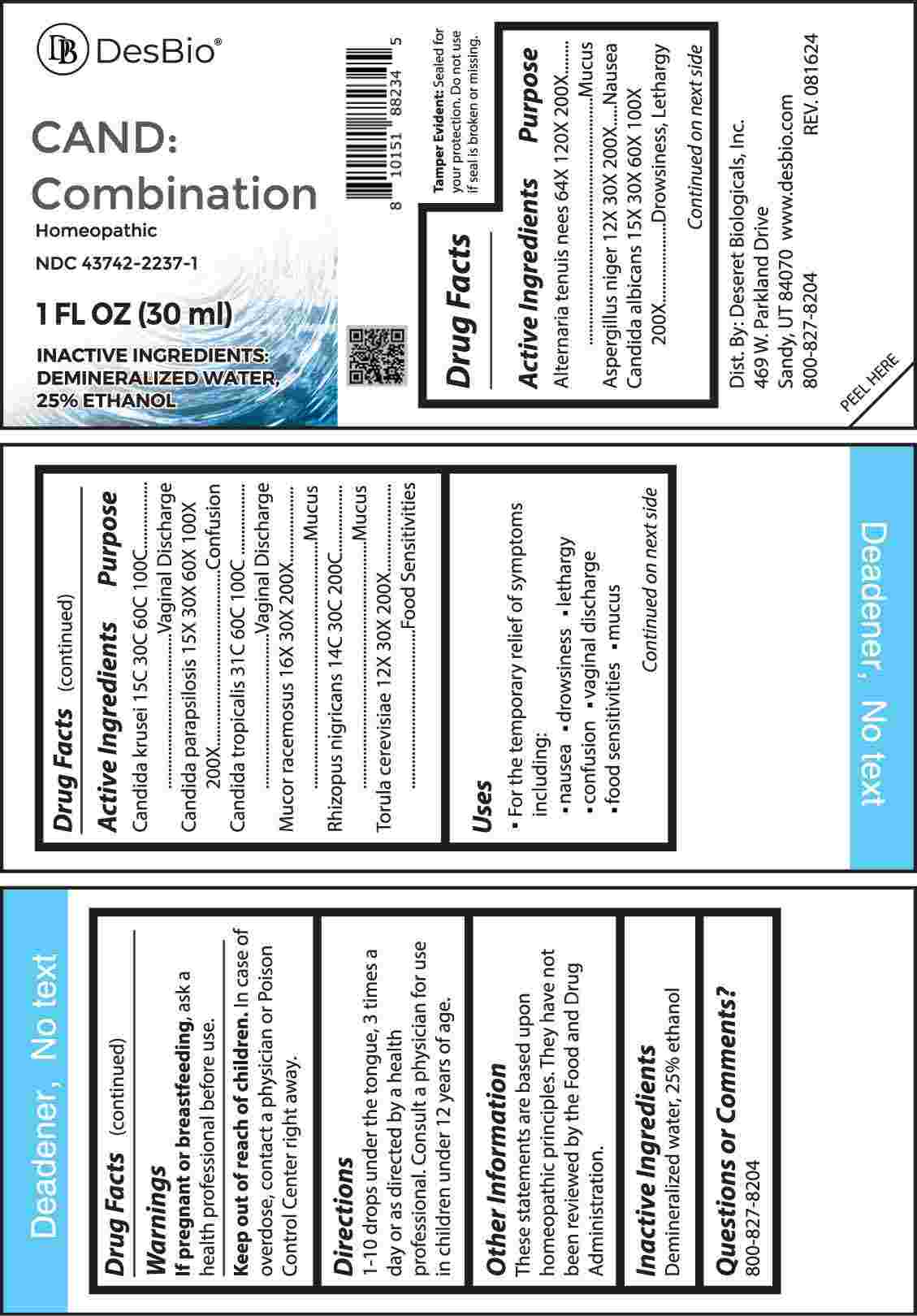 DRUG LABEL: Cand Combination
NDC: 43742-2237 | Form: LIQUID
Manufacturer: Deseret Biologicals, Inc.
Category: homeopathic | Type: HUMAN OTC DRUG LABEL
Date: 20241111

ACTIVE INGREDIENTS: ALTERNARIA ALTERNATA 64 [hp_X]/1 mL; ASPERGILLUS NIGER VAR. NIGER 12 [hp_X]/1 mL; CANDIDA ALBICANS 15 [hp_X]/1 mL; ISSATCHENKIA ORIENTALIS WHOLE 15 [hp_C]/1 mL; CANDIDA PARAPSILOSIS 15 [hp_X]/1 mL; CANDIDA TROPICALIS 31 [hp_C]/1 mL; MUCOR RACEMOSUS 16 [hp_X]/1 mL; RHIZOPUS STOLONIFER 14 [hp_C]/1 mL; SACCHAROMYCES CEREVISIAE 12 [hp_X]/1 mL
INACTIVE INGREDIENTS: WATER; ALCOHOL

DRUG FACTS:

ACTIVE INGREDIENTS:

Alternaria Tenuis Nees 64X, 120X, 200X, Aspergillus Niger 12X, 30X, 200X, Candida Albicans 15X, 30X, 60X, 100X, 200X, Candida Krusei 15C, 30C, 60C, 100C, Candida Parapsilosis 15X, 30X, 60X, 100X, 200X, Candida Tropicalis 31C, 60C, 100C, Mucor Racemosus 16X, 30X, 200X, Rhizopus Nigricans 14C, 30C, 200C, Torula Cerevisiae 12X, 30X, 200X.

PURPOSE:

Alternaria Tenuis Nees - Mucus, Aspergillus Niger - Nausea, Candida Albicans – Drowsiness, Lethargy, Candida Krusei – Vaginal Discharge, Candida Parapsilosis - Confusion, Candida Tropicalis – Vaginal Discharge, Mucor Racemosus - Mucus, Rhizopus Nigricans - Mucus, Torula Cerevisiae – Food Sensitivities

USES:

• For the temporary relief of symptoms including:

• nausea • drowsiness • lethargy • confusion

• vaginal discharge • food sensitivities • mucus

These statements are based upon homeopathic principles. They have not been reviewed by the Food and Drug Administration.

WARNINGS:

If pregnant or breast-feeding, ask a health professional before use.

Keep out of reach of children. In case of overdose, contact a physician or Poison Control Center right away.

Tamper Evident: Sealed for your protection. Do not use if seal is broken or missing.

KEEP OUT OF REACH OF CHILDREN:

In case of overdose, contact a physician or Poison Control Center right away.

DIRECTIONS:

1-10 drops under the tongue, 3 times a day or as directed by a health professional. Consult a physician for use in children under 12 years of age.

INACTIVE INGREDIENTS:

Demineralized water, 25% ethanol

QUESTIONS:

Dist. By: Deseret Biologicals, Inc.

469 W. Parkland Drive

Sandy, UT 84070

www.desbio.com

800-827-8204

PACKAGE LABEL DISPLAY:

DesBio

CAND:Combination

Homeopathic
NDC 43742-2237-1
1 FL OZ (30 ml)